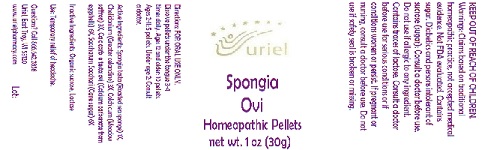 DRUG LABEL: Spongia Ovi
NDC: 48951-8203 | Form: PELLET
Manufacturer: Uriel Pharmacy Inc.
Category: homeopathic | Type: HUMAN OTC DRUG LABEL
Date: 20180607

ACTIVE INGREDIENTS: SPONGIA OFFICINALIS SKELETON, ROASTED 1 [hp_X]/1 1; CHELIDONIUM MAJUS 3 [hp_X]/1 1; COLCHICUM AUTUMNALE WHOLE 3 [hp_X]/1 1; CALCIUM CARBONATE 6 [hp_X]/1 1; SUGARCANE 6 [hp_X]/1 1
INACTIVE INGREDIENTS: SUCROSE

Spongia Ovi

INDICATIONS AND USAGE

Directions: FOR ORAL USE ONLY.

DOSAGE AND ADMINISTRATION

Dissolve pellets under the tongue 3-4 times daily. Ages 12 and older: 10 pellets. Ages 2-11: 5 pellets. Under age 2: Consult a doctor.

ACTIVE INGREDIENT

Active Ingredients: Spongia tosta (Roasted sea sponge) 1X, Chelidonium (Greater celandine) 3X, Colchicum (Meadow saffron) 3X, Calc carb. e testa ovi (Calcium carbonate from eggshells) 6X, Saccharum Sacchari (Cane sugar) 6X

Inactive Ingredient: Organic sucrose

PURPOSE

Use: Temporary relief of headache.

KEEP OUT OF REACH OF CHILDREN.

WARNINGS

Warnings: Claims based on traditional homeopathic practice, not accepted medical evidence. Not FDA evaluated. Contains sugar. Diabetics and persons intolerant of sucrose (sugar): Consult a doctor before use. Do not use if allergic to any ingredient. Contains traces of lactose. Consult a doctor before use for serious conditions or if conditions worsen or persist. If pregnant or nursing, consult a doctor before use. Do not use if safety seal is broken or missing.

QUESTIONS

Questions? Call 866.642.2858 Uriel, East Troy, WI 53120 www.urielpharmacy.com